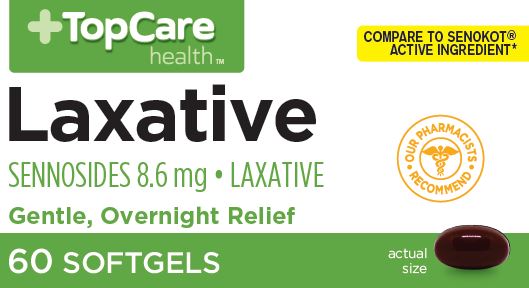 DRUG LABEL: SENNA
NDC: 36800-135 | Form: CAPSULE
Manufacturer: TOP CARE (Topco Associates LLC)
Category: otc | Type: HUMAN OTC DRUG LABEL
Date: 20241220

ACTIVE INGREDIENTS: SENNOSIDES 8.6 mg/1 1
INACTIVE INGREDIENTS: SILICON DIOXIDE; YELLOW WAX; POVIDONE K30; FD&C RED NO. 40; FD&C YELLOW NO. 6; FD&C BLUE NO. 1; GELATIN; GLYCERIN; MINERAL OIL; CARBOXYMETHYLCELLULOSE SODIUM; SORBITOL SOLUTION; LECITHIN, SOYBEAN; TITANIUM DIOXIDE; WATER

Topcare Laxative - Sennosides 8.6mg

Active ingredient (in each softgel)

Sennosides 8.6 mg

Purpose

Laxative

Uses

- relieves occasional constipation (irregularity)
- generally produces a bowel movement in 6-12 hours

Warnings

Do not use

- laxative products for longer than 1 week unless directed by a doctor

Ask a doctor before using if you have

- stomach pain
- nausea
- vomiting
- noticed a sudden change in bowel habits that continues over a period of 2 weeks.

Stop use and ask a doctor if

you have rectal bleeding or fail to have a bowel movement after use of a laxative. These may indicate a serious condition.

If pregnant or breast-feeding,

ask a health professional before use.

Keep out of reach of children.

In case of overdose, get medical help or contact a Poison Control Center right away.

Directions

- take preferably at bedtime or as directed by a doctor

age | starting dosage | maximum dosage
adults and children 12 years of age and over | 2 tablets once a day | 4 tablets twice a day
children 6 to under 12 years | 1 tablet once a day | 2 tablets twice a day
children 2 to under 6 years | 1/2 tablet once a day | 1 tablet twice a day
children under 2 years | ask a doctor | ask a doctor

Other information

- each tablet contains: calcium 1mg and sodium less than 1mg
- store at 25oC (77o F); excursions permitted between 15_30oC (59_86oF)

Inactive Ingredients

aerosil, beeswax, FD&C Blue No. 1, FD&C Red No.40, FD&C Yellow No. 6, gelatin, glycerin,
light liquid paraffin, povidone (PVP K-30), purified water, sodium carboxymethyl cellulose,
sorbitol solution, soya lecithin, titanium dioxide

Questions or comments?

1-888-333-9792

Principal Display Panel

TopCare health™

COMPARE TO SENOKOT® ACTIVE INGREDIENT*

Laxative

SENNOSIDES 8.6 mg • LAXATIVE

Gentle, Overnight Relief

60 SOFTGELS

actual size